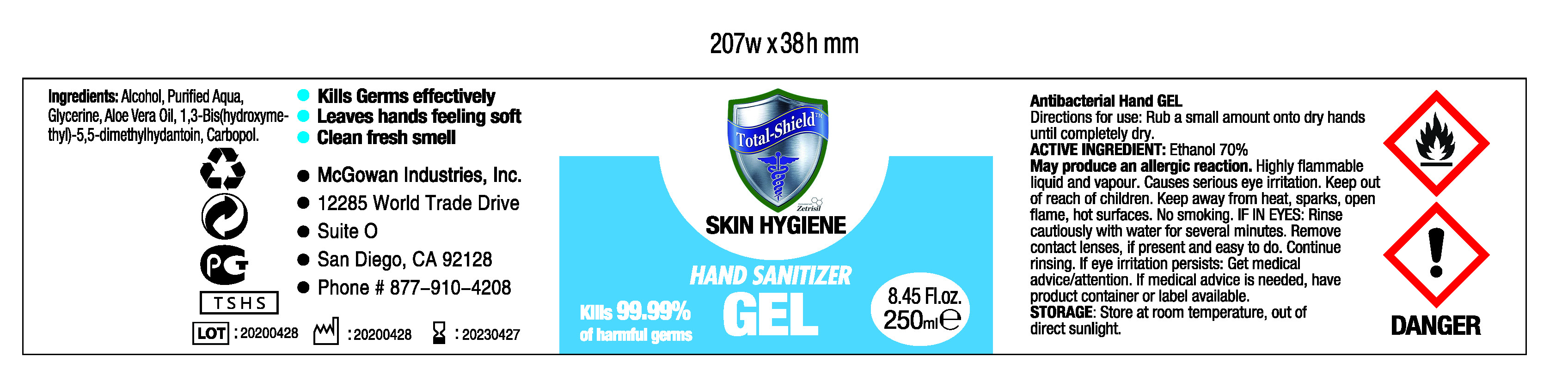 DRUG LABEL: Total-Shield Hand Sanitizer Gel
NDC: 79365-170 | Form: GEL
Manufacturer: YANGZHOU WEIDELI TRADING CO., LTD.
Category: otc | Type: HUMAN OTC DRUG LABEL
Date: 20200701

ACTIVE INGREDIENTS: ALCOHOL 70 mL/100 mL
INACTIVE INGREDIENTS: WATER; GLYCERIN; ALOE VERA LEAF; DMDM HYDANTOIN; CARBOMER HOMOPOLYMER, UNSPECIFIED TYPE

Active Ingredient

Ethanol 70%

Purpose

Antiseptic, Hand Sanitizer

Use

Hand Sanitizer to help reduce bacteria that potentially can cause disease. For use when soap and water are not available.

Warnings

May produce an allergic reaction. Highly flammable liquid and vapour. Causes serious eye irritation. Keep out of reach of children. Keep away from heat, sparks, open flame, hot surfaces. No smoking. IF IN EYES: Rinse cautiously with water for several minutes. Remove contact lenses, if present and easy to do. Continue rinsing. If eye irritation persists: Get medical advice/attention. If medical advice is needed, have product container or label available

Keep out of reach of children

Directions for use

Rub a small amount onto dry hands until completely dry.

Storage

Store at room temperature, out of direct sunlight.

Ingredients:

Alcohol, Purified Aqua, Glycerine, Aloe Vera Oil, 1,3-Bis(hydroxymethyl)-5,5-dimethylhydantoin, Carbopol.

PACKAGE LABEL

250 mL